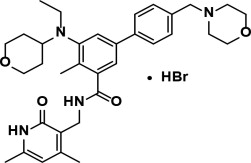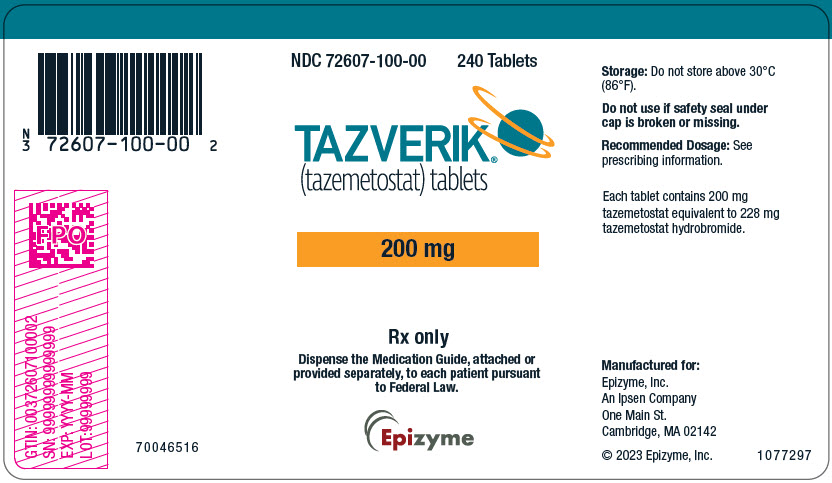 DRUG LABEL: TAZVERIK
NDC: 72607-100 | Form: TABLET, FILM COATED
Manufacturer: Epizyme, Inc.
Category: prescription | Type: HUMAN PRESCRIPTION DRUG LABEL
Date: 20240815

ACTIVE INGREDIENTS: tazemetostat hydrobromide 200 mg/1 1
INACTIVE INGREDIENTS: Lactose monohydrate; Low-substituted hydroxypropyl cellulose, unspecified; Hydroxypropyl cellulose, unspecified; Sodium starch glycolate Type A potato; Magnesium stearate; Hypromellose, unspecified; Talc; Polyethylene glycol 8000; Titanium dioxide; Ferric oxide red

HIGHLIGHTS OF PRESCRIBING INFORMATION

These highlights do not include all the information needed to use TAZVERIK® safely and effectively. See full prescribing information for TAZVERIK.
TAZVERIK (tazemetostat) tablets, for oral use
Initial U.S. Approval: 2020

RECENT MAJOR CHANGES

Dosage and Administration, Modifications for Drug Interactions (2.4) | 08/2024
Warnings and Precautions, Secondary Malignancies (5.1) | 11/2023

1 INDICATIONS AND USAGE

TAZVERIK is a methyltransferase inhibitor indicated for the treatment of:

- Adults and pediatric patients aged 16 years and older with metastatic or locally advanced epithelioid sarcoma not eligible for complete resection. (1.1)
- Adult patients with relapsed or refractory follicular lymphoma whose tumors are positive for an EZH2 mutation as detected by an FDA-approved test and who have received at least 2 prior systemic therapies. (1.2)
- Adult patients with relapsed or refractory follicular lymphoma who have no satisfactory alternative treatment options. (1.2)

These indications are approved under accelerated approval based on overall response rate and duration of response. Continued approval for these indications may be contingent upon verification and description of clinical benefit in a confirmatory trial(s).

2 DOSAGE AND ADMINISTRATION

- Recommended dosage is 800 mg taken orally twice daily with or without food. (2.2)

3 DOSAGE FORMS AND STRENGTHS

Tablets: 200 mg (3)

4 CONTRAINDICATIONS

None. (4)

5 WARNINGS AND PRECAUTIONS

- Secondary Malignancies: TAZVERIK increases the risk of developing secondary malignancies, including T-cell lymphoblastic lymphoma, myelodysplastic syndrome, acute myeloid leukemia, and B-cell acute lymphoblastic leukemia. Monitor patients long-term for the development of secondary malignancies. (5.1)
- Embryo-Fetal Toxicity: Can cause fetal harm. Advise patients of potential risk to a fetus and to use effective non-hormonal contraception. (5.2)

6 ADVERSE REACTIONS

- The most common (≥20%) adverse reactions in patients with epithelioid sarcoma are pain, fatigue, nausea, decreased appetite, vomiting, and constipation. (6.1)
- The most common (≥20%) adverse reactions in patients with follicular lymphoma are fatigue, upper respiratory tract infection, musculoskeletal pain, nausea, and abdominal pain. (6.1)

To report SUSPECTED ADVERSE REACTIONS, contact Epizyme at 855-463-5127 or FDA at 1-800-FDA-1088 or www.fda.gov/medwatch.

7 DRUG INTERACTIONS

- Strong or Moderate Cytochrome P450 (CYP)3A Inhibitors: Avoid coadministration of strong or moderate CYP3A inhibitors with TAZVERIK. Reduce the dose of TAZVERIK if coadministration of strong or moderate CYP3A inhibitors cannot be avoided. (2.3, 7.1)
- Strong or Moderate CYP3A Inducers: Avoid coadministration with TAZVERIK. (7.1)

8 USE IN SPECIFIC POPULATIONS

- Lactation: Advise not to breastfeed. (8.2)

FULL PRESCRIBING INFORMATION

1 INDICATIONS AND USAGE

1.1 Epithelioid Sarcoma

TAZVERIK is indicated for the treatment of adults and pediatric patients aged 16 years and older with metastatic or locally advanced epithelioid sarcoma not eligible for complete resection.

This indication is approved under accelerated approval based on overall response rate and duration of response [see Clinical Studies (14.1)]. Continued approval for this indication may be contingent upon verification and description of clinical benefit in a confirmatory trial(s).

1.2 Relapsed or Refractory Follicular Lymphoma

- TAZVERIK is indicated for the treatment of adult patients with relapsed or refractory (R/R) follicular lymphoma (FL) whose tumors are positive for an EZH2 mutation as detected by an FDA-approved test and who have received at least 2 prior systemic therapies.
- TAZVERIK is indicated for the treatment of adult patients with R/R FL who have no satisfactory alternative treatment options.

These indications are approved under accelerated approval based on overall response rate and duration of response [see Clinical Studies (14.2)]. Continued approval for these indications may be contingent upon verification and description of clinical benefit in a confirmatory trial(s).

2 DOSAGE AND ADMINISTRATION

2.1 Patient Selection

Select patients with R/R FL for treatment with TAZVERIK based on the presence of EZH2 mutation of codons Y646, A682, or A692 in tumor specimens [see Clinical Studies (14.2)]. Information on FDA-approved tests for the detection of EZH2 mutation in relapsed or refractory follicular lymphoma is available at: http://www.fda.gov/CompanionDiagnostics.

2.2 Recommended Dosage

The recommended dosage of TAZVERIK is 800 mg orally twice daily with or without food until disease progression or unacceptable toxicity.

Swallow tablets whole. Do not cut, crush, or chew tablets.

Do not take an additional dose if a dose is missed or vomiting occurs after TAZVERIK, but continue with the next scheduled dose.

2.3 Dosage Modifications for Adverse Reactions

Table 1 summarizes the recommended dose reductions, and Table 2 summarizes the recommended dosage modifications of TAZVERIK for adverse reactions.

Table 1. Recommended Dose Reductions of TAZVERIK for Adverse Reactions
Dose Reduction | Dosage
First | 600 mg orally twice daily
Second | 400 mg orally twice daily*
*Permanently discontinue TAZVERIK in patients who are unable to tolerate 400 mg orally twice daily.

Table 2. Recommended Dosage Modifications of TAZVERIK for Adverse Reactions
Adverse Reaction | Severity | Dosage Modification
Neutropenia [see Adverse Reactions (6.1)] | Neutrophil count less than 1 × 10^9/L | - Withhold until neutrophil count is greater than or equal to 1 × 10^9/L or baseline. - For first occurrence, resume at same dose. - For second and third occurrence, resume at reduced dose. - Permanently discontinue after fourth occurrence.
Thrombocytopenia [see Adverse Reactions (6.1)] | Platelet count less than 50 × 10^9/L | - Withhold until platelet count is greater than or equal to 75 × 10^9/L or baseline. - For first and second occurrence, resume at reduced dose. - Permanently discontinue after third occurrence.
Anemia [see Adverse Reactions (6.1)] | Hemoglobin less than 8 g/dL | - Withhold until improvement to at least Grade 1 or baseline, then resume at same or reduced dose.
Other adverse reactions [see Adverse Reactions (6.1)] | Grade 3 | - Withhold until improvement to at least Grade 1 or baseline. - For first and second occurrence, resume at reduced dose. - Permanently discontinue after third occurrence.
Other adverse reactions [see Adverse Reactions (6.1)] | Grade 4 | - Withhold until improvement to at least Grade 1 or baseline. - For first occurrence, resume at reduced dose. - Permanently discontinue after second occurrence.

2.4 Dosage Modifications for Drug Interactions

Strong or Moderate CYP3A Inhibitors

Avoid coadministration of TAZVERIK with strong or moderate CYP3A inhibitors. If coadministration with a strong or moderate CYP3A inhibitor cannot be avoided, reduce the TAZVERIK dose as shown in Table 3 below. After discontinuation of the strong or moderate CYP3A inhibitor for 3 elimination half-lives, resume the TAZVERIK dose that was taken prior to initiating the inhibitor [see Drug Interactions (7.1), Clinical Pharmacology (12.3)].

Table 3. Recommended Dose Reductions of TAZVERIK for Strong or Moderate CYP3A Inhibitors
Current Dosage | Adjusted Dosage
800 mg orally twice daily | 400 mg orally twice daily
600 mg orally twice daily | 400 mg for first dose and 200 mg for second dose
400 mg orally twice daily | 200 mg orally twice daily

3 DOSAGE FORMS AND STRENGTHS

Tablets: 200 mg film-coated, red, round, biconvex shape and debossed with "EZM 200" on one side and plain on the other.

4 CONTRAINDICATIONS

None.

5 WARNINGS AND PRECAUTIONS

5.1 Secondary Malignancies

The risk of developing secondary malignancies is increased following treatment with TAZVERIK. Across clinical trials of 758 adults who received TAZVERIK 800 mg twice daily as monotherapy, myelodysplastic syndrome (MDS), acute myeloid leukemia (AML), or B-cell acute lymphoblastic leukemia (B-ALL) occurred in 1.7% of patients. One pediatric patient developed T-cell lymphoblastic lymphoma (T-LBL). Monitor patients long-term for the development of secondary malignancies.

5.2 Embryo-Fetal Toxicity

Based on findings from animal studies and its mechanism of action, TAZVERIK can cause fetal harm when administered to pregnant women. There are no available data on TAZVERIK use in pregnant women to inform the drug-associated risk. Administration of tazemetostat to pregnant rats and rabbits during organogenesis resulted in dose-dependent increases in skeletal developmental abnormalities in both species beginning at maternal exposures approximately 1.5 times the adult human exposure (area under the plasma concentration time curve [AUC0-45h]) at the 800 mg twice daily dose.

Advise pregnant women of the potential risk to a fetus. Advise females of reproductive potential to use effective contraception during treatment with TAZVERIK and for 6 months after the final dose. Advise males with female partners of reproductive potential to use effective contraception during treatment with TAZVERIK and for 3 months after the final dose [see Use in Specific Populations (8.1, 8.3)].

6 ADVERSE REACTIONS

The following clinically significant adverse reactions are described elsewhere in labeling:

- Secondary Malignancies [see Warnings and Precautions (5.1)].

6.1 Clinical Trial Experience

Because clinical trials are conducted under widely varying conditions, adverse reaction rates observed in the clinical trials of a drug cannot be directly compared with rates in the clinical trials of another drug and may not reflect the rates observed in practice.

Epithelioid Sarcoma

The safety of TAZVERIK was evaluated in a cohort (Cohort 5) of Study EZH-202 that enrolled patients with epithelioid sarcoma [see Clinical Studies (14.1)]. Patients received TAZVERIK 800 mg orally twice daily (n=62). Among patients who received TAZVERIK, 44% were exposed for 6 months or longer and 24% were exposed for greater than one year.

Serious adverse reactions occurred in 37% of patients who received TAZVERIK. Serious adverse reactions in ≥3% of patients who received TAZVERIK were hemorrhage, pleural effusion, skin infection, dyspnea, pain, and respiratory distress.

One patient (2%) permanently discontinued TAZVERIK due to an adverse reaction of altered mood.

Dosage interruptions due to an adverse reaction occurred in 34% of patients who received TAZVERIK. The most frequent adverse reactions requiring dosage interruptions in ≥3% were hemorrhage, increased alanine aminotransferase (ALT), and increased aspartate aminotransferase (AST).

Dose reduction due to an adverse reaction occurred in one (2%) patient who received TAZVERIK; the dose was reduced in this patient for decreased appetite.

The most common adverse reactions (≥20%) were pain, fatigue, nausea, decreased appetite, vomiting, and constipation.

Table 4 presents adverse reactions in patients with epithelioid sarcoma in Cohort 5 of Study EZH-202.

Table 4. Adverse Reactions (≥10%) in Patients with Epithelioid Sarcoma Who Received TAZVERIK in Cohort 5 of Study EZH-202
Adverse Reaction | TAZVERIK N=62
Adverse Reaction | All Grades (%) | Grade 3 or 4 (%)
General
Paina | 52 | 7
Fatigueb | 47 | 1.6
Gastrointestinal
Nausea | 36 | 0
Vomiting | 24 | 0
Constipation | 21 | 0
Diarrhea | 16 | 0
Abdominal painc | 13 | 1.6
Metabolism and nutrition
Decreased appetite | 26 | 4.8
Respiratory, thoracic and mediastinal
Cough | 18 | 0
Dyspnead | 16 | 4.8
Vascular
Hemorrhagee | 18 | 4.8
Nervous system
Headache | 18 | 0
Investigations
Weight decreased | 16 | 7
a Includes tumor pain, pain in extremity, non-cardiac chest pain, flank pain, back pain, arthralgia, bone pain, cancer pain, musculoskeletal pain, myalgia, neck pain
b Includes fatigue and asthenia
c Includes abdominal pain, gastrointestinal pain, abdominal pain lower
d Includes dyspnea and dyspnea exertional
e Includes wound hemorrhage, rectal hemorrhage, pulmonary hemorrhage, hemorrhage intracranial, cerebral hemorrhage, hemoptysis

Table 5 summarizes select laboratory abnormalities in patients with epithelioid sarcoma in Cohort 5 of Study EZH-202.

Table 5. Select Laboratory Abnormalities (≥ 10%) Worsening from Baseline in Patients with Epithelioid Sarcoma Who Received TAZVERIK in Cohort 5 of Study EZH-202
Laboratory Abnormality | TAZVERIK*
Laboratory Abnormality | All Grades (%) | Grade 3 or 4 (%)
Hematology
Decreased hemoglobin | 49 | 15
Decreased lymphocytes | 36 | 13
Decreased white blood cell count | 19 | 0
Chemistry
Increased triglycerides | 36 | 3.3
Increased glucose | 33 | 1.6
Decreased sodium | 30 | 1.7
Decreased phosphate | 28 | 1.7
Decreased albumin | 23 | 0
Increased alkaline phosphatase | 23 | 1.7
Decreased potassium | 20 | 1.7
Increased aspartate aminotransferase | 18 | 3.5
Decreased calcium | 16 | 0
Decreased glucose | 16 | 0
Increased partial thromboplastin time | 15 | 5
Increased alanine aminotransferase | 14 | 3.4
Increased creatinine | 12 | 0
Increased potassium | 12 | 0
*The denominator used to calculate the rate varied from 39 to 61 based on the number of patients with a baseline value and at least one post-treatment value.

Relapsed or Refractory Follicular Lymphoma

The safety of TAZVERIK was evaluated in two cohorts (Cohorts 4 and 5) of Study E7438-G000-101 that enrolled patients with relapsed or refractory follicular lymphoma [see Clinical Studies (14.2)]. Patients received TAZVERIK 800 mg orally twice daily (n=99). Among patients who received TAZVERIK, 68% were exposed for 6 months or longer, 39% were exposed for 12 months or longer, and 21% were exposed for 18 months or longer.

The median age was 62 years (range 36 to 87 years), 54% were male, and 95% had an Eastern Cooperative Oncology Group (ECOG) performance status of 0-1. The median number of prior therapies was 3 (range 1 to 11). Patients were required to have a creatinine clearance ≥40 mL/min per the Cockcroft and Gault formula.

Serious adverse reactions occurred in 30% of patients who received TAZVERIK. Serious adverse reactions in ≥2% of patients who received TAZVERIK were general physical health deterioration, abdominal pain, pneumonia, sepsis, and anemia.

Permanent discontinuation due to an adverse reaction occurred in 8% of patients who received TAZVERIK. Adverse reaction resulting in permanent discontinuation in ≥2% of patients was second primary malignancy.

Dosage interruptions due to an adverse reaction occurred in 28% of patients who received TAZVERIK. Adverse reactions requiring dosage interruptions in ≥3% of patients were thrombocytopenia and fatigue.

Dose reduction due to an adverse reaction occurred in 9% of patients who received TAZVERIK.

The most common adverse reactions (≥20%) were fatigue, upper respiratory tract infection, musculoskeletal pain, nausea, and abdominal pain.

Table 6 presents adverse reactions in patients with relapsed or refractory follicular lymphoma in Cohorts 4 and 5 of Study E7438-G000-101.

Table 6. Adverse Reactions (≥10%) in Patients with Relapsed or Refractory Follicular Lymphoma Who Received TAZVERIK in Cohorts 4 and 5 of Study E7438-G000-101
Adverse Reaction | TAZVERIK N=99
Adverse Reaction | All Grades (%) | Grade 3 or 4 (%)
General
Fatiguea | 36 | 5
Pyrexia | 10 | 0
Infections
Upper respiratory tract infectionb | 30 | 0
Lower respiratory tract infectionc | 17 | 0
Urinary tract infectiond | 11 | 2
Gastrointestinal
Nausea | 24 | 1
Abdominal paine | 20 | 3
Diarrhea | 18 | 0
Vomiting | 12 | 1
Musculoskeletal and connective tissue
Musculoskeletal painf | 22 | 1
Skin and subcutaneous tissue
Alopecia | 17 | 0
Rashg | 15 | 0
Respiratory and mediastinal system
Coughh | 17 | 0
Nervous system
Headachei | 13 | 0
a Includes fatigue and asthenia
b Includes laryngitis, nasopharyngitis, pharyngitis, rhinitis, sinusitis, upper respiratory tract infection, viral upper respiratory tract infection
c Includes bronchitis, lower respiratory tract infection, tracheobronchitis
d Includes cystitis, urinary tract infection, urinary tract infection staphylococcal
e Includes abdominal discomfort, abdominal pain, abdominal pain lower, abdominal pain upper
f Includes back pain, limb discomfort, musculoskeletal chest pain, musculoskeletal discomfort, musculoskeletal pain, myalgia, neck pain, non-cardiac chest pain, pain in extremity, pain in jaw, spinal pain
g Includes erythema, rash, rash erythematous, rash generalized, rash maculo-papular, rash pruritic, rash pustular, skin exfoliation
h Includes cough and productive cough
i Includes headache, migraine, sinus headache

Clinically relevant adverse reactions occurring in <10% of patients who received TAZVERIK included:

- Infection: sepsis (2%), pneumonia (2%), and herpes zoster (2%)

Table 7 summarizes select laboratory abnormalities in patients with follicular lymphoma in Cohorts 4 and 5 of Study E7438-G000-101.

Table 7. Select Laboratory Abnormalities (≥10%) Worsening from Baseline in Patients with Relapsed or Refractory Follicular Lymphoma Who Received TAZVERIK in Cohorts 4 and 5 of Study E7438-G000-101
Laboratory Abnormality | TAZVERIK*
Laboratory Abnormality | All Grades (%) | Grade 3 or 4 (%)
Hematology
Decreased lymphocytes | 57 | 18
Decreased hemoglobin | 50 | 8
Decreased platelets | 50 | 7
Decreased white blood cells | 41 | 9
Decreased neutrophils | 20 | 7
Chemistry
Increased glucose | 53 | 10
Increased aspartate aminotransferase | 24 | 0
Increased alanine aminotransferase | 21 | 2.3
Increased alkaline phosphatase | 18 | 1.0
Increased creatinine | 17 | 0
*The denominator used to calculate the rate varied from 88 to 96 based on the number of patients with a baseline value and at least one post-treatment value.

7 DRUG INTERACTIONS

7.1 Effect of Other Drugs on TAZVERIK

Strong or Moderate CYP3A Inhibitors

Coadministration of TAZVERIK with a strong or moderate CYP3A inhibitor increases tazemetostat plasma concentrations [see Clinical Pharmacology (12.3)], which may increase the frequency or severity of adverse reactions. Avoid coadministration of strong or moderate CYP3A inhibitors with TAZVERIK. If coadministration of strong or moderate CYP3A inhibitors cannot be avoided, reduce TAZVERIK dose [see Dosage and Administration (2.4)].

Strong or Moderate CYP3A Inducers

Coadministration of TAZVERIK with a strong CYP3A inducer decreases tazemetostat plasma concentrations [see Clinical Pharmacology (12.3)], and coadministration of TAZVERIK with a moderate CYP3A inducer may also decrease tazemetostat plasma concentrations. The decrease in tazemetostat plasma concentration may decrease the efficacy of TAZVERIK. Avoid coadministration of moderate or strong CYP3A inducers with TAZVERIK.

7.2 Effect of TAZVERIK on Other Drugs

CYP3A Substrates

Coadministration of TAZVERIK with CYP3A substrates, including hormonal contraceptives, can result in decreased concentrations and reduced efficacy of CYP3A substrates [see Use in Specific Populations (8.3), Clinical Pharmacology (12.3)].

8 USE IN SPECIFIC POPULATIONS

8.1 Pregnancy

Risk Summary

Based on findings from animal studies and its mechanism of action [see Clinical Pharmacology (12.1)], TAZVERIK can cause fetal harm when administered to pregnant women. There are no available data on TAZVERIK use in pregnant women to inform the drug-associated risk. Administration of tazemetostat to pregnant rats and rabbits during organogenesis resulted in dose-dependent increases in skeletal developmental abnormalities in both species beginning at maternal exposures approximately 1.5 times the adult human exposure [AUC0-45h] at the 800 mg twice daily dose (see Data). Advise pregnant women of the potential risk to a fetus.

In the U.S. general population, the estimated background risk of major birth defects and miscarriage in clinically recognized pregnancies is 2% to 4% and 15% to 20%, respectively.

Data

Animal Data

In pregnant rats, once daily oral administration of tazemetostat during the period of organogenesis from gestation day (GD) 7 through 17 resulted in no maternal adverse effects at doses up to 100 mg/kg/day (approximately 6 times the adult human exposure at 800 mg twice daily). Skeletal malformations and variations occurred in fetuses at doses of ≥50 mg/kg (approximately 2 times the adult human exposure at the 800 mg twice daily dose). At 200 mg/kg (approximately 14 times the adult human exposure at the 800 mg twice daily dose), major findings included increased post implantation loss, missing digits, fused vertebrae, domed heads and fused bones of the skull, and reduced fetal body weights.

In pregnant rabbits, no adverse maternal effects were observed after once daily oral administration of 400 mg/kg/day tazemetostat (approximately 7 times the adult human exposure at the 800 mg twice daily dose) from GD 7 through 19. Skeletal variations were present at doses ≥100 mg/kg/day (approximately 1.5 times the adult human exposure at the 800 mg twice daily dose), with skeletal malformations at ≥200 mg/kg/day (approximately 5.6 times the adult human exposure at the 800 mg twice daily dose). At 400 mg/kg (approximately 7 times the adult human exposure at the 800 mg twice daily dose), major findings included increased post implantation loss and cleft palate and snout.

8.2 Lactation

Risk Summary

There are no animal or human data on the presence of tazemetostat in human milk or on its effects on the breastfed child or milk production. Because of the potential risk for serious adverse reactions from TAZVERIK in the breastfed child, advise women not to breastfeed during treatment with TAZVERIK and for one week after the final dose.

8.3 Females and Males of Reproductive Potential

Pregnancy Testing

Verify the pregnancy status of females of reproductive potential prior to initiating TAZVERIK [see Use in Specific Populations (8.1)].

Risk Summary

TAZVERIK can cause fetal harm when administered to pregnant women [see Use in Specific Populations (8.1)].

Contraception

Females

Advise females of reproductive potential to use effective non-hormonal contraception during treatment with TAZVERIK and for 6 months after the final dose. TAZVERIK can render some hormonal contraceptives ineffective [see Drug Interactions (7.2)].

Males

Advise males with female partners of reproductive potential to use effective contraception during treatment with TAZVERIK and for at least 3 months after the final dose.

8.4 Pediatric Use

The safety and effectiveness of TAZVERIK have been established in pediatric patients aged 16 years and older (adolescents) with metastatic or locally advanced epithelioid sarcoma. Use of TAZVERIK for this indication is supported by evidence from adequate and well-controlled studies in adults (including 3 adolescent patients aged 16 years) [see Adverse Reactions (6.1), Clinical Pharmacology (12.3), Clinical Studies (14.1)].

The safety and effectiveness of TAZVERIK in pediatric patients aged less than 16 years have not been established.

Juvenile Animal Toxicity Data

In a 13-week juvenile rat toxicology study, animals were dosed daily from post-natal day 7 to day 97 (approximately equivalent to neonate to adulthood). Tazemetostat resulted in:

- T-LBL at doses ≥50 mg/kg (approximately 2.8 times the adult human exposure at the 800 mg twice daily dose)
- Increased trabecular bone at doses ≥100 mg/kg (approximately 10 times the adult human exposure at the 800 mg twice daily dose)
- Increased body weight at doses ≥50 mg/kg (approximately equal to the adult human exposure at the 800 mg twice daily dose)
- Distended testicles in males at doses ≥50 mg/kg (approximately equal to the adult human exposure at the 800 mg twice daily dose)

8.5 Geriatric Use

Clinical studies of TAZVERIK did not include sufficient numbers of patients with epithelioid sarcoma or relapsed or refractory follicular lymphoma aged 65 and over to determine whether they respond differently from younger subjects.

8.6 Renal Impairment

No dose adjustment of TAZVERIK is recommended for patients with mild to severe renal impairment or end stage renal disease [see Clinical Pharmacology (12.3)].

8.7 Hepatic Impairment

No dose adjustment of TAZVERIK is recommended for patients with mild hepatic impairment (total bilirubin > 1 to 1.5 times upper limit of normal [ULN] or AST > ULN). TAZVERIK has not been studied in patients with moderate (total bilirubin > 1.5 to 3 times ULN) or severe (total bilirubin > 3 times ULN) hepatic impairment [see Clinical Pharmacology (12.3)].

11 DESCRIPTION

Tazemetostat is a methyltransferase inhibitor. Tazemetostat hydrobromide has the following chemical name: [1,1'-Biphenyl]-3-carboxamide, N-[(1,2-dihydro-4,6-dimethyl-2-oxo-3-pyridinyl)methyl]-5-[ethyl(tetrahydro-2H-pyran-4-yl)amino]-4-methyl-4'-(4-morpholinylmethyl)-, hydrobromide (1:1). The molecular formula of tazemetostat hydrobromide is C34H44N4O4∙HBr. Tazemetostat hydrobromide has a molecular weight of 653.66 g/mol and the following structural formula:

Tazemetostat hydrobromide is a white to off-white solid that is slightly soluble in water and has pKa values of 5.26, 6.88, and 12.62. A saturated aqueous solution of tazemetostat hydrobromide has a pH of approximately 5 at ambient conditions.

TAZVERIK (tazemetostat) tablets for oral use contain 200 mg tazemetostat, equivalent to 228 mg tazemetostat hydrobromide.

Each tablet is film-coated and contains the following inactive ingredients in the tablet core: hydroxypropyl cellulose, lactose monohydrate, low-substituted hydroxypropyl cellulose, magnesium stearate, and sodium starch glycolate. The film-coat contains hypromellose, polyethylene glycol, red iron oxide, talc, and titanium dioxide.

12 CLINICAL PHARMACOLOGY

12.1 Mechanism of Action

Tazemetostat is an inhibitor of the methyltransferase, EZH2, and some EZH2 gain-of-function mutations including Y646X, A682G, and A692V. Tazemetostat also inhibited EZH1 with a half-maximal inhibitory concentration (IC50) of 392 nM, approximately 36 times higher than the IC50 for inhibition of EZH2.

The most well-characterized function of EZH2 is as the catalytic subunit of the polycomb repressive complex 2 (PRC2), catalyzing mono-, di-, and trimethylation of lysine 27 of histone H3. Trimethylation of histone H3 leads to transcriptional repression.

SWItch/Sucrose Non-Fermentable (SWI/SNF) complexes can antagonize PRC2 function in the regulation of the expression of certain genes of patients with epithelioid sarcoma. Preclinical in vitro and in vivo models with the loss or dysfunction of certain SWI/SNF complex members (e.g., integrase interactor 1 [INI1/SNF5/SMARCB1/BAF47], SMARCA4, and SMARCA2) can lead to aberrant EZH2 activity or expression and a resulting oncogenic dependence on EZH2.

Tazemetostat suppressed proliferation of B-cell lymphoma cell lines in vitro and demonstrated antitumor activity in a mouse xenograft model of B-cell lymphoma with or without EZH2 gain-of-function mutations. Tazemetostat demonstrated greater effects on the inhibition of proliferation of lymphoma cell lines with mutant EZH2.

12.2 Pharmacodynamics

Tazemetostat exposure-response relationships and the time course of pharmacodynamic responses are unknown.

Cardiac Electrophysiology

The effect of orally administered TAZVERIK, at doses ranging from 100 mg to 1600 mg twice daily (0.125 to 2 times the approved recommended dosage) for 15 days, on the heart-rate corrected QT (QTc) interval was evaluated in a dose-finding study in 38 patients with advanced malignancies. Tazemetostat and its metabolite EPZ-6930 did not cause a large mean increase (i.e. >20 ms) on the QTc interval at the 800 mg twice daily dose. The largest mean increase (upper bound of 90% confidence interval) in QTc were 6.1 ms (8.5 ms) and 9.3 ms (12.5 ms) at a dose of 800 mg twice daily and 1600 mg twice daily, respectively.

12.3 Pharmacokinetics

The systemic exposure of tazemetostat is approximately dose proportional over the dose range of 200 mg to 1600 mg twice daily of TAZVERIK (0.25 to 2 times the approved recommended dosage). Following TAZVERIK 800 mg orally twice daily, steady-state was reached by Day 15. The mean (coefficient of variation [CV]%) steady-state peak plasma concentration (Cmax) was 829 (56%) ng/mL and AUC0-12h was 3340 (49%) ng•h/mL. Tazemetostat exhibited time-dependent pharmacokinetics (PK). The mean accumulation ratio (measured by AUC) was 0.58.

Absorption

The mean absolute oral bioavailability of tazemetostat is approximately 33%. The median time to reach the peak plasma concentration of tazemetostat is 1 to 2 hours.

Effect of Food

A high-fat, high-calorie (approximately 800 to 1000 calories) meal does not have a significant effect on tazemetostat exposure.

Distribution

The mean (CV%) apparent volume of distribution at steady-state (Vss/F) is 1230 L (46%). Tazemetostat is 88% bound to human plasma proteins in vitro. The blood-to-plasma ratio is 0.73.

Elimination

At steady-state, the estimated mean (CV%) terminal elimination half-life of tazemetostat is 3.1 hours (14%) and the apparent total clearance (CLss/F) is 274 L/h (49%).

Metabolism

In vitro, tazemetostat is metabolized by CYP3A to form the inactive major metabolites M5 (EPZ-6930) and M3 (EPZ006931). M5 undergoes further metabolism by CYP3A.

Excretion

Following a single oral dose of radiolabeled tazemetostat, 94% of the total radioactivity was recovered over 12 days, with 15% excreted into urine and 79% into feces.

Specific Populations

Age (16 to 91 years), sex, race (White, Black, Asian), body weight (37.3 to 173 kg), mild hepatic impairment (total bilirubin > 1 to 1.5 times ULN or AST > ULN) and renal impairment, including end stage renal disease, have no clinically meaningful effect on the pharmacokinetics of tazemetostat. The effect of moderate to severe hepatic impairment has not been studied.

Drug Interaction Studies

Clinical Studies

Effect of CYP3A Inhibitors on Tazemetostat:

Coadministration of fluconazole (a moderate CYP3A inhibitor) with TAZVERIK 400 mg twice daily in patients increased tazemetostat steady-state AUC0-8h by 3.1-fold and Cmax by 2.3-fold.

Coadministration of itraconazole (a strong CYP3A inhibitor) with TAZVERIK 400 mg twice daily in patients increased tazemetostat steady-state AUC0-12h by 2.5-fold and Cmax by 1.9-fold.

Effect of CYP3A Inducers on Tazemetostat

Coadministration of rifampin (a strong CYP3A inducer) with TAZVERIK 800 mg twice daily in patients decreased tazemetostat steady-state AUC0-12h by 84% and Cmax by 84%. Coadministration of tazemetostat with a moderate CYP3A inducer is also predicted to decrease tazemetostat plasma concentrations, which may decrease the efficacy of tazemetostat.

Effect of Gastric Acid Reducing Agents on Tazemetostat:

Coadministration of omeprazole (a proton pump inhibitor) with TAZVERIK 800 mg twice daily in patients increased tazemetostat steady-state AUC0-8h by 26% and Cmax by 25%, which is not expected to have clinically relevant impact.

Effect of Tazemetostat on CYP3A Substrate:

Coadministration of TAZVERIK 800 mg twice daily with oral midazolam (a sensitive CYP3A substrate) in patients decreased midazolam AUC0-12h by 40% and Cmax by 21%.

Effect of Tazemetostat on CYP2C8 and CYP2C19 Substrates:

Coadministration of TAZVERIK 800 mg twice daily with repaglinide (a sensitive CYP2C8 substrate) and omeprazole (a sensitive CYP2C19 substrate) in patients increased repaglinide AUC0-8h by 80% and Cmax by 51%; and had no effect on the exposure of omeprazole.

In Vitro Studies

Metabolic Enzymes:

Tazemetostat does not inhibit CYP1A2, CYP2B6, CYP2C9, and CYP2D6 at clinically relevant concentrations.

Drug Transporters:

Tazemetostat is a substrate of p-glycoprotein (P-gp). Tazemetostat is not a substrate of breast cancer resistance protein (BCRP); renal transporters organic cation transporter 2 (OCT2), organic anion transporter 3 (OAT3), and multidrug and toxin extrusion transporter 1 (MATE1); or hepatic transporters organic anion transporting polypeptide 1B1 (OATP1B1) and organic anion transporting polypeptide 1B3 (OATP1B3).

Tazemetostat is an inhibitor of MATE1 and multidrug and toxin extrusion transporter 2-K (MATE2-K). Tazemetostat does not inhibit P-gp, BCRP, OATP1B1, OATP1B3, organic cation transporter 1 (OCT1), OCT2, organic anion transporter 1 (OAT1), OAT3, or bile salt export pump (BSEP) at clinically relevant concentrations.

13 NONCLINICAL TOXICOLOGY

13.1 Carcinogenesis, Mutagenesis, Impairment of Fertility

Dedicated carcinogenicity studies were not conducted with tazemetostat, but T-LBL, MDS, AML, and B-ALL have been reported clinically and T-LBL occurred in juvenile and adult rats after ~9 or more weeks of tazemetostat administration during 13-week toxicity studies. Based on nonclinical studies in rats, the risk of T-LBL appears to be greater with longer duration dosing.

Tazemetostat did not cause genetic damage in a standard battery of studies including a screening and pivotal bacterial reverse mutation (Ames) assay, an in vitro micronucleus assessment in human peripheral blood lymphocytes, and an in vivo micronucleus assessment in rats after oral administration.

Fertility and early embryonic development studies have not been conducted with tazemetostat; however, assessments of male and female reproductive organs were included in 4- and 13-week repeat-dose toxicity studies in rats and cynomolgus monkeys. Oral daily administration of tazemetostat did not result in any notable effects in the adult male and female reproductive organs [see Use in Specific Populations (8.3)].

14 CLINICAL STUDIES

14.1 Epithelioid Sarcoma

The efficacy of TAZVERIK was evaluated in an open-label, single-arm cohort (Cohort 5) of a multi-center study (Study EZH-202, NCT02601950) in patients with histologically confirmed, metastatic or locally advanced epithelioid sarcoma. Patients were required to have INI1 loss, detected using local tests, and an Eastern Cooperative Oncology Group (ECOG) performance status (PS) of 0-2. Patients received TAZVERIK 800 mg orally twice daily until disease progression or unacceptable toxicity. Tumor response assessments were performed every 8 weeks. The major efficacy outcome measures were confirmed overall response rate (ORR) according to Response Evaluation Criteria in Solid Tumors (RECIST) v1.1 as assessed by blinded independent central review (BICR) and duration of response (DOR). Median duration of follow-up was 14 months (range 0.4 to 31).

Among the 62 patients who received TAZVERIK, median age was 34 years (range 16 to 79); 63% were male, 76% were White, 11% were Asian, 44% had proximal disease, 92% had an ECOG PS of 0 or 1, and 8% had an ECOG PS of 2. Prior surgery occurred in 77% of patients; 61% received prior systemic chemotherapy.

Efficacy results are summarized in Table 8.

Table 8. Efficacy Results for Patients with Epithelioid Sarcoma Enrolled in Cohort 5 of Study EZH-202
Efficacy Endpoints | TAZVERIK N=62
Overall Response Rate (95% CI)* | 15% (7%, 26%)
Complete Response | 1.6%
Partial Response | 13%
Duration of Response
% with duration ≥ 6 months | 67%
Range in months | 3.7, 24.5+
CI = Confidence Interval
*Time to response ranged from 1.4 to 18.4 months.

14.2 Relapsed or Refractory Follicular Lymphoma

The efficacy of TAZVERIK was evaluated in two open-label, single-arm cohorts (Cohorts 4 and 5) of a multi-center study (Study E7438-G000-101, NCT01897571) in patients with histologically confirmed follicular lymphoma after at least 2 prior systemic therapies. Patients were required to have ECOG PS of 0-2 and were enrolled based on EZH2 mutation status. EZH2 mutations were identified prospectively using formalin-fixed, paraffin-embedded tumor samples, which were centrally tested using the cobas® EZH2 Mutation Test; the cobas EZH2 Mutation test is designed to detect the following mutations: Y646X [S,H,C], Y646F, Y646N, A682G, and A692V. Patients received TAZVERIK 800 mg orally twice daily until confirmed disease progression or unacceptable toxicity. Tumor response assessments were performed every 8 weeks through Week 24 and then every 12 weeks. The major efficacy outcome measures were ORR and DOR according to the International Working Group Non-Hodgkin Lymphoma (IWG-NHL) criteria^1 as assessed by Independent Review Committee. Median duration of follow-up was 22 months (range 3 months to 44 months) for patients with EZH2 MT positive tumors and 36 months (range 32 months to 39 months) for patients whose tumors did not have an EZH2 mutation detected.

A total of 99 patients were enrolled, including 45 patients whose tumors had one of these EZH2 mutations (mutant) and 54 patients whose tumors did not have one of these mutations (wild-type).

Among the 45 patients with EZH2 mutant follicular lymphoma, median age was 62 years (range 38 to 80), 58% were female, 42% had early progression following front-line therapy (POD24), and all had an ECOG PS of 0
or 1. Race was reported in 84% of patients; of these patients, 82% were White. Based on the cobas EZH2 Mutation test, 36%, 29%, 27%, 11% and 2% of patients had the following mutations: Y646X [S,H,C], Y646F, Y646N, A682G, and A692V, respectively. The median number of lines of prior systemic therapy was 2 (range 1 to 11), with 49% refractory to rituximab, 49% refractory to their last therapy, and 9% had received prior stem cell transplant.

Among the 54 patients with EZH2 wild-type follicular lymphoma, median age was 61 years (range 36 to 87), 63% were male, 59% had POD24, and 91% had an ECOG PS of 0 or 1. Race was reported in 57% of patients; of these patients, 48% were White and 3% were Asian. The median number of lines of prior systemic therapy was 3 (range 1 to 8), with 59% refractory to rituximab, 41% refractory to their last therapy, and 39% had received prior stem cell transplant.

The approval of TAZVERIK was based upon the efficacy in 95 patients (42 EZH2 Mutant, 53 EZH2 Wild-Type) who had received at least 2 prior systemic therapies and is presented in Table 9.

Table 9. Efficacy Results for Patients with Relapsed or Refractory Follicular Lymphoma Enrolled into Cohorts 4 and 5 of Study E7438-G000-101
Efficacy Endpoints | TAZVERIK N=95
Efficacy Endpoints | EZH2 Mutant Follicular Lymphoma N=42 | EZH2 Wild-Type Follicular Lymphoma N=53
Overall Response Rate (95% CI)* | 69% (53%, 82%) | 34% (22%, 48%)
Complete Response | 12% | 4%
Partial Response | 57% | 30%
Duration of Response
Median (95% CI) in months | 10.9 (7.2, NE) | 13.0 (5.6, NE)
Range in months | 0.0+, 22.1+ | 1, 22.5+
CI = Confidence Interval; NE = Not Estimable.
*Median time to response for patients with EZH2 MT follicular lymphoma was 3.7 months (range 1.6 to 10.9) and for patients with EZH2 WT follicular lymphoma was 3.9 months (range 1.6 to 16.3).

15 REFERENCES

1. Cheson BD, Pfistner B, Juweid ME, et al. Revised response criteria for malignant lymphoma. J Clin Oncol. 2007;25(5):579-586.

16 HOW SUPPLIED/STORAGE AND HANDLING

TAZVERIK 200 mg film-coated tablets are red, round, biconvex shape and debossed with "EZM 200" on one side and plain on the other. TAZVERIK is available in:

Bottles of 240 tablets with a desiccant; NDC 72607-100-00

Do not store above 30°C (86°F).

17 PATIENT COUNSELING INFORMATION

Advise the patient to read the FDA-approved patient labeling (Medication Guide).

Secondary Malignancies

Advise patients of the increased risk of secondary hematologic malignancies. Advise patients to inform their healthcare provider if they experience fatigue, easy bruising, fever, bone pain, or paleness [see Warnings and Precautions (5.1)].

Embryo-Fetal Toxicity

Advise pregnant women and females of reproductive potential of the potential risk to a fetus. Advise females to inform their healthcare provider of a known or suspected pregnancy [see Use in Specific Populations (8.1)].

Advise females of reproductive potential to use effective non-hormonal contraception during treatment with TAZVERIK and for 6 months after the final dose [see Use in Specific Populations (8.3)].

Advise males with female partners of reproductive potential to use effective contraception during treatment with TAZVERIK and for 3 months after the final dose [see Use in Specific Populations (8.3), Nonclinical Toxicology (13.1)].

Lactation

Advise women not to breastfeed during treatment with TAZVERIK and for 1 week after the final dose [see Use in Special Populations (8.2)].

Drug Interactions

Advise patients and caregivers to inform their healthcare provider of all concomitant medications, including prescription medicines, over-the-counter drugs, vitamins, and herbal products. Inform patients to avoid St. John's wort, grapefruit, and grapefruit juice while taking TAZVERIK [see Drug Interactions (7.1)].

Manufactured for:
Epizyme, Inc.
An Ipsen Company
One Main St.
Cambridge, MA 02142

©2023, 2024 Epizyme, Inc.

MEDICATION GUIDE
TAZVERIK® (taz vayr′ ik)
(tazemetostat)
tablets

What is the most important information I should know about TAZVERIK?
TAZVERIK can cause serious side effects, including:

- Risk of new cancers. An increase in new (second) cancers has happened in people who were treated with TAZVERIK. Talk with your healthcare provider about your risk of developing new cancers. Your healthcare provider will monitor you for new cancers after your treatment with TAZVERIK. Tell your healthcare provider if you are more tired than usual, or have easy bruising, fever, bone pain, or paleness.

See "What are the possible side effects of TAZVERIK" for more information about side effects.

What is TAZVERIK?
TAZVERIK is a prescription medicine used to treat:

- adults and children aged 16 years and older with epithelioid sarcoma that has spread or grown and cannot be removed by surgery.
- adults with follicular lymphoma when the disease has come back or did not respond to treatment, whose tumors have an abnormal EZH2 gene, and who have been treated with at least two prior medicines. Your healthcare provider will perform a test to make sure TAZVERIK is right for you.
- adults with follicular lymphoma when the disease has come back or did not respond to treatment, who have no other satisfactory treatment options.

It is not known if TAZVERIK is safe and effective in children less than 16 years of age.

Before taking TAZVERIK tell your healthcare provider about all of your medical conditions, including if you:

- are pregnant or plan to become pregnant. TAZVERIK can harm your unborn baby. Your healthcare provider will give you a pregnancy test before you start treatment with TAZVERIK. Tell your healthcare provider right away if you become pregnant or think you may be pregnant.
  - Females who are able to become pregnant should use effective non-hormonal birth control (such as condoms) during treatment and for 6 months after the final dose of TAZVERIK. Birth control pills (oral contraceptives) and other hormonal forms of birth control may not be effective if used during treatment with TAZVERIK. Talk to your healthcare provider about birth control options that are right for you.
  - Males with female partners who are able to become pregnant should use effective birth control during treatment and for 3 months after the final dose of TAZVERIK.
- are breastfeeding or plan to breastfeed. It is not known if TAZVERIK passes into your breast milk. Do not breastfeed during treatment and for 1 week after the final dose of TAZVERIK.

Tell your healthcare provider about all the medicines you take, including prescription and over-the-counter medicines, vitamins, and herbal supplements. TAZVERIK may affect the way other medicines work and other medicines may affect how TAZVERIK works.

How should I take TAZVERIK?

- Take TAZVERIK exactly as your healthcare provider tells you.
- Take TAZVERIK 2 times each day.
- Take TAZVERIK with or without food.
- Swallow TAZVERIK tablets whole. Do not cut, crush, or chew tablets.
- If you miss a dose or vomit after taking your dose, just skip that dose and take the next dose at your regular time.
- Your healthcare provider may change your dose, temporarily stop, or completely stop treatment with TAZVERIK if you get certain side effects.

What should I avoid while taking TAZVERIK?

- Avoid eating grapefruit or drinking grapefruit juice during treatment with TAZVERIK.
- Avoid taking St. John's wort during treatment with TAZVERIK.

What are the possible side effects of TAZVERIK?
TAZVERIK can cause serious side effects. See "What is the most important information I should know about TAZVERIK?"
The most common side effects of TAZVERIK in people with epithelioid sarcoma include:

- pain

- nausea

- vomiting

- tiredness

- decreased appetite

- constipation

The most common side effects of TAZVERIK in people with follicular lymphoma include:

- tiredness

- bone and muscle pain

- cold-like symptoms (upper respiratory infection)

- nausea

- stomach (abdominal) pain

These are not all the possible side effects of TAZVERIK.
Call your doctor for medical advice about side effects. You may report side effects to FDA at 1-800-FDA-1088.

How should I store TAZVERIK?
Do not store TAZVERIK tablets above 86°F (30°C).
Keep TAZVERIK and all medicines out of the reach of children.

General information about the safe and effective use of TAZVERIK.
Medicines are sometimes prescribed for purposes other than those listed in a Medication Guide. Do not use TAZVERIK for a condition for which it was not prescribed. Do not give TAZVERIK to other people, even if they have the same symptoms that you have. It may harm them. You can ask your pharmacist or healthcare provider for information about TAZVERIK that is written for health professionals.

What are the ingredients in TAZVERIK?
Active Ingredient: tazemetostat.
Inactive Ingredients: Tablet core: hydroxypropyl cellulose, lactose monohydrate, low-substituted hydroxypropyl cellulose, magnesium stearate, and sodium starch glycolate. Film-coating: hypromellose, polyethylene glycol, red iron oxide, talc, and titanium dioxide.
Manufactured for: Epizyme, Inc.
An Ipsen Company
One Main St.
Cambridge, MA 02142 For more information, contact Epizyme at 855-463-5127.

This Medication Guide has been approved by the U.S. Food and Drug Administration.

Issued: November/2023

Principal Display Panel - 200 mg Bottle Label

NDC 72607-100-00

240 Tablets

TAZVERIK®
(tazemetostat) tablets

200 mg

Rx only

Dispense the Medication Guide, attached or
provided separately, to each patient pursuant
to Federal Law.

Epizyme